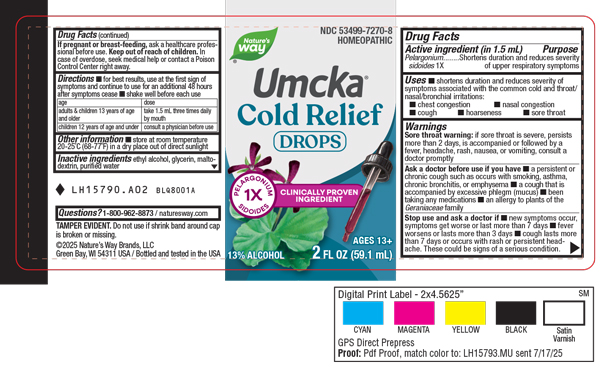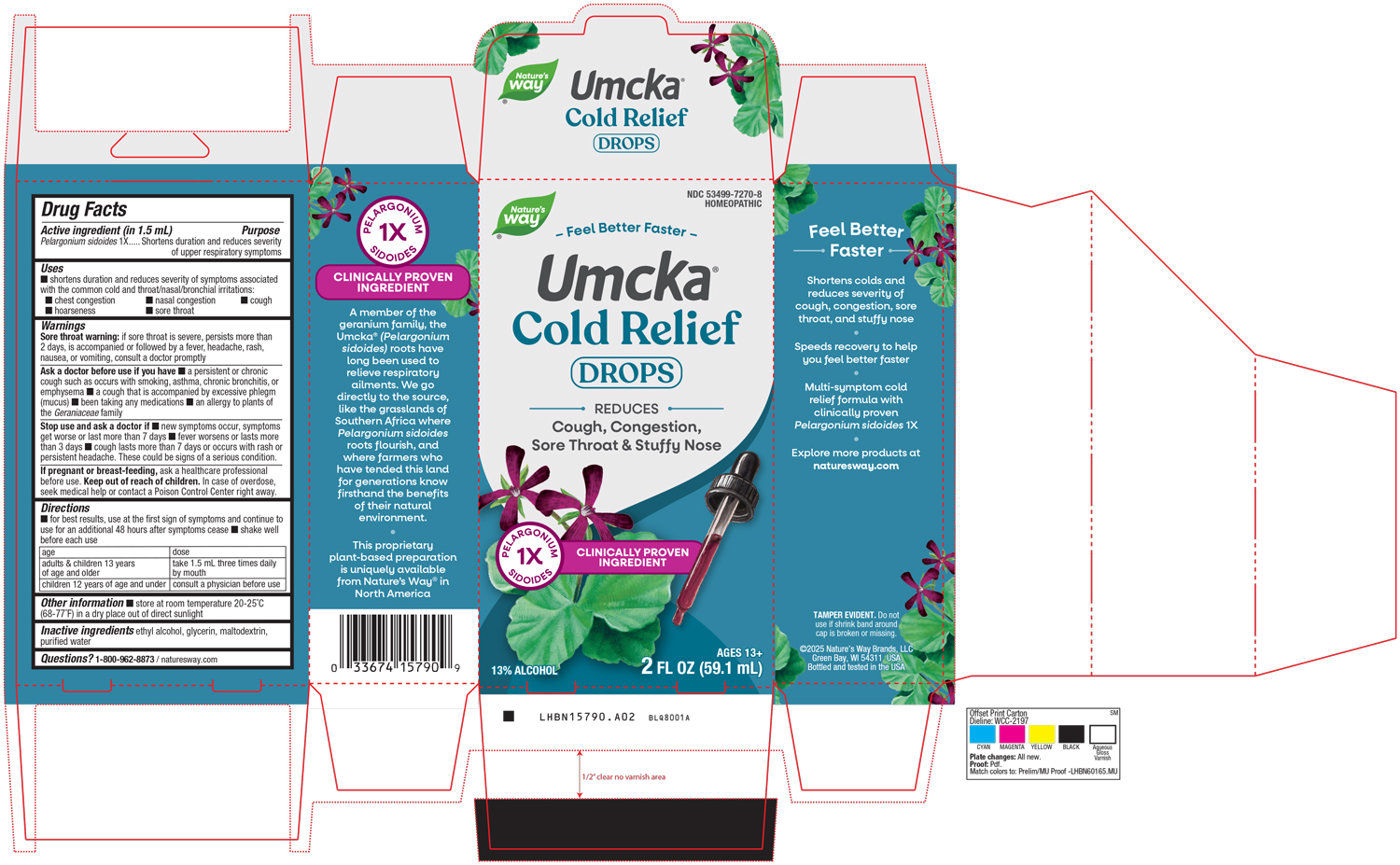 DRUG LABEL: Cold Relief
NDC: 53499-7270 | Form: LIQUID
Manufacturer: Schwabe North America
Category: homeopathic | Type: HUMAN OTC DRUG LABEL
Date: 20251002

ACTIVE INGREDIENTS: PELARGONIUM SIDOIDES ROOT 1 [hp_X]/30 mL
INACTIVE INGREDIENTS: ALCOHOL; MALTODEXTRIN; GLYCERIN; WATER

Cold Relief Drops

Active Ingredient

Pelargonium sidoides 1X

Inactive Ingredient

Ethyl Alcohol

Glycerin

Maltodextrin

Purified Water

Dosage & Administation

Directions:

For best results, use at the first sign of symptoms and continue to use for an additional 48 hours after symptoms cease.

Shake well before each use.

Adults & children 13 years of age and older: take 1.5 mL three times daily by mouth.

Children 12 years of age and under: consult a physician before use.

Indications & Usage

Shortens duration and reduces severity of symptoms associated with the common cold and throat/nasal/bronchial irritations: chest congestion, nasal congestion, cough, hoarseness, sore throat.

Purpose

Shortens duration and reduces severity of symptoms associated with the common cold and throat/nasal/bronchial irritations: chest congestion, nasal congestion, cough, hoarseness, sore throat.

Warnings

Sore throat warning: if sore throat is severe, persists more than 2 days, is accompanied or followed by a fever, headache, rash, nausea, or vomiting, consult a doctor promptly.

Ask Doctor

Ask a doctor before use if you have a persistent or chronic cough such as occurs with smoking, asthma, chronic bronchitis, or emphysema, a cough that is accompanied by excessive phlegm (mucus), been taking any medications, an allergy to plants of the Geraniaceae family.

Stop Use

Stop use and ask a doctor if new symptoms occur, symptoms get worse or last more than 7 days, fever worsens or lasts more than 3 days, cough lasts more than 7 days or occurs with rash or persistent headache.

These could be signs of a serious condition.

Pregnancy or Breast-Feeding

If pregnant or breast-feeding, ask a healthcare professional before use.

Keep out of reach of children

Overdosage

In case of overdose, seek medical help or contact a Poison Control Center right away.